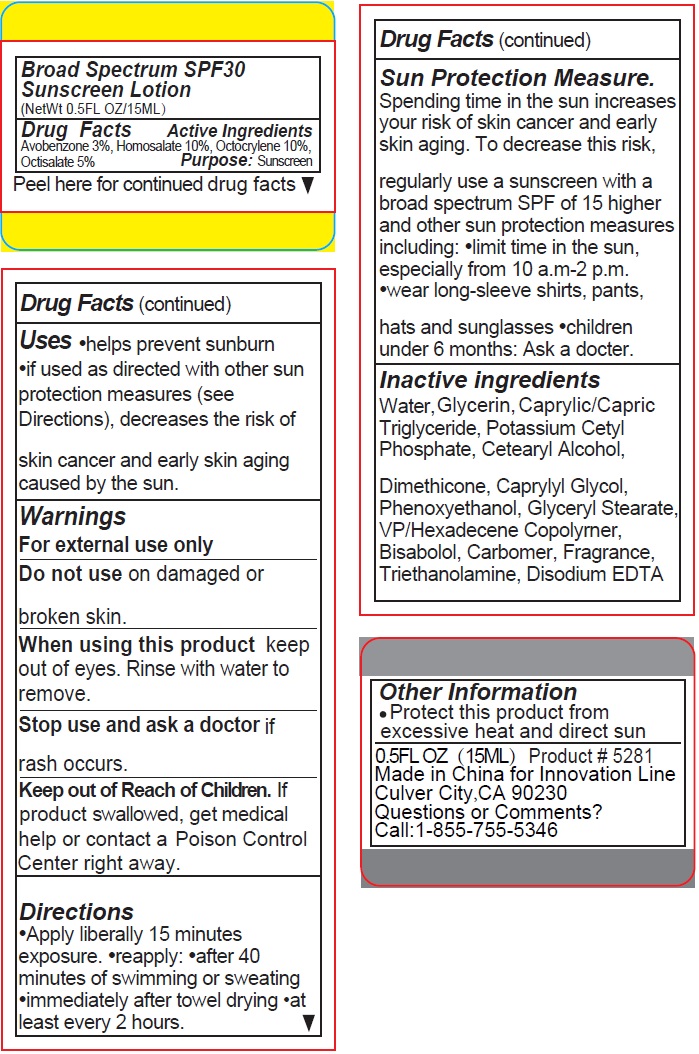 DRUG LABEL: 5281 SUNSCREEN
NDC: 76138-219 | Form: LOTION
Manufacturer: Innovation Specialties
Category: otc | Type: HUMAN OTC DRUG LABEL
Date: 20240710

ACTIVE INGREDIENTS: AVOBENZONE 30 mg/1 mL; HOMOSALATE 100 mg/1 mL; OCTOCRYLENE 100 mg/1 mL; OCTISALATE 50 mg/1 mL
INACTIVE INGREDIENTS: WATER; GLYCERIN; MEDIUM-CHAIN TRIGLYCERIDES; POTASSIUM CETYL PHOSPHATE; CETOSTEARYL ALCOHOL; DIMETHICONE; CAPRYLYL GLYCOL; PHENOXYETHANOL; GLYCERYL MONOSTEARATE; VINYLPYRROLIDONE/HEXADECENE COPOLYMER; LEVOMENOL; CARBOMER HOMOPOLYMER, UNSPECIFIED TYPE; TROLAMINE; EDETATE DISODIUM ANHYDROUS

5281 SUNSCREEN

Active Ingredients

Avobenzone 3%, Homosalate 10%, Octocrylene 10%, Octisalate 5%

Purpose:

Sunscreen

Uses

•helps prevent sunburn
•if used as directed with other sun protection measures (see Directions), decreases the risk of skin cancer and early skin aging caused by the sun.

Warnings

For external use only

Do not useon damaged or broken skin.

When using this productkeep out of eyes. Rinse with water to remove.

Stop use and ask a doctorif rash occurs.

Keep out of Reach of Children.If product swallowed, get medical help or contact a Poison Control Center right away.

Directions

•Apply liberally 15 minutes exposure. •reapply: •after 40 minutes of swimming or sweating •immediately after towel drying •at least every 2 hours.

Sun Protection Measure.
Spending time in the sun increases your risk of skin cancer and early skin aging. To decrease this risk, regularly use a sunscreen with a broad spectrum SPF of 15 higher and other sun protection measures including: •limit time in the sun, especially from 10 a.m-2 p.m. •wear long-sleeve shirts, pants, hats and sunglasses •children under 6 months: Ask a doctor.

Inactive ingredients

Water, Glycerin, Caprylic/Capric Triglyceride, Potassium Cetyl Phosphate, Cetearyl Alcohol, Dimethicone, Caprylyl Glycol, Phenoxyethanol, Glyceryl Stearate, VP/Hexadecene Copolymer, Bisabolol, Carbomer, Fragrance, Triethanolamine, Disodium EDTA

Other Information

•Protect this product from excessive heat and direct sun

Questions or Comments?

Call:1-855-755-5346

Broad Spectrum SPF30

Product # 5281
Made in China for Innovation Line
Culver City, CA 90230